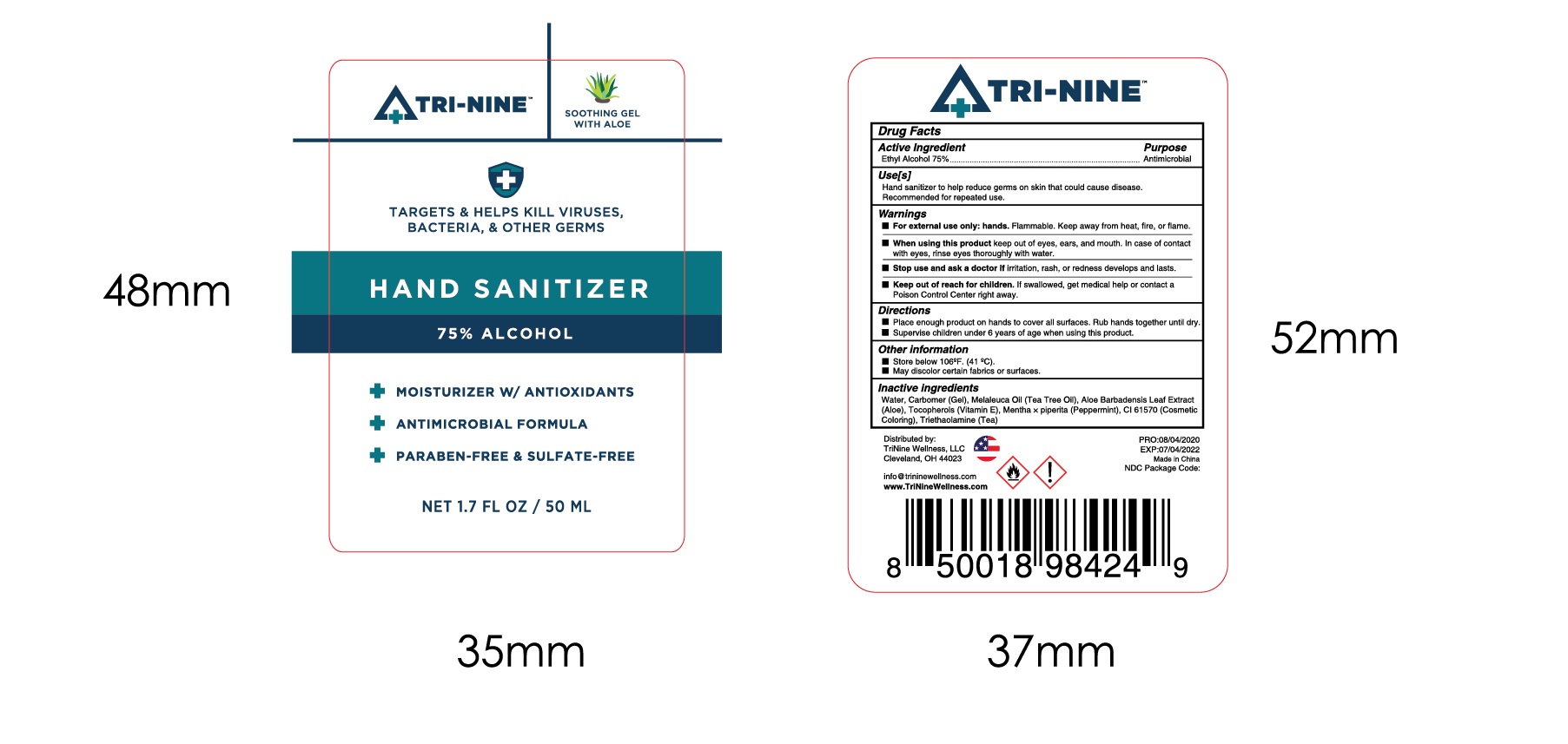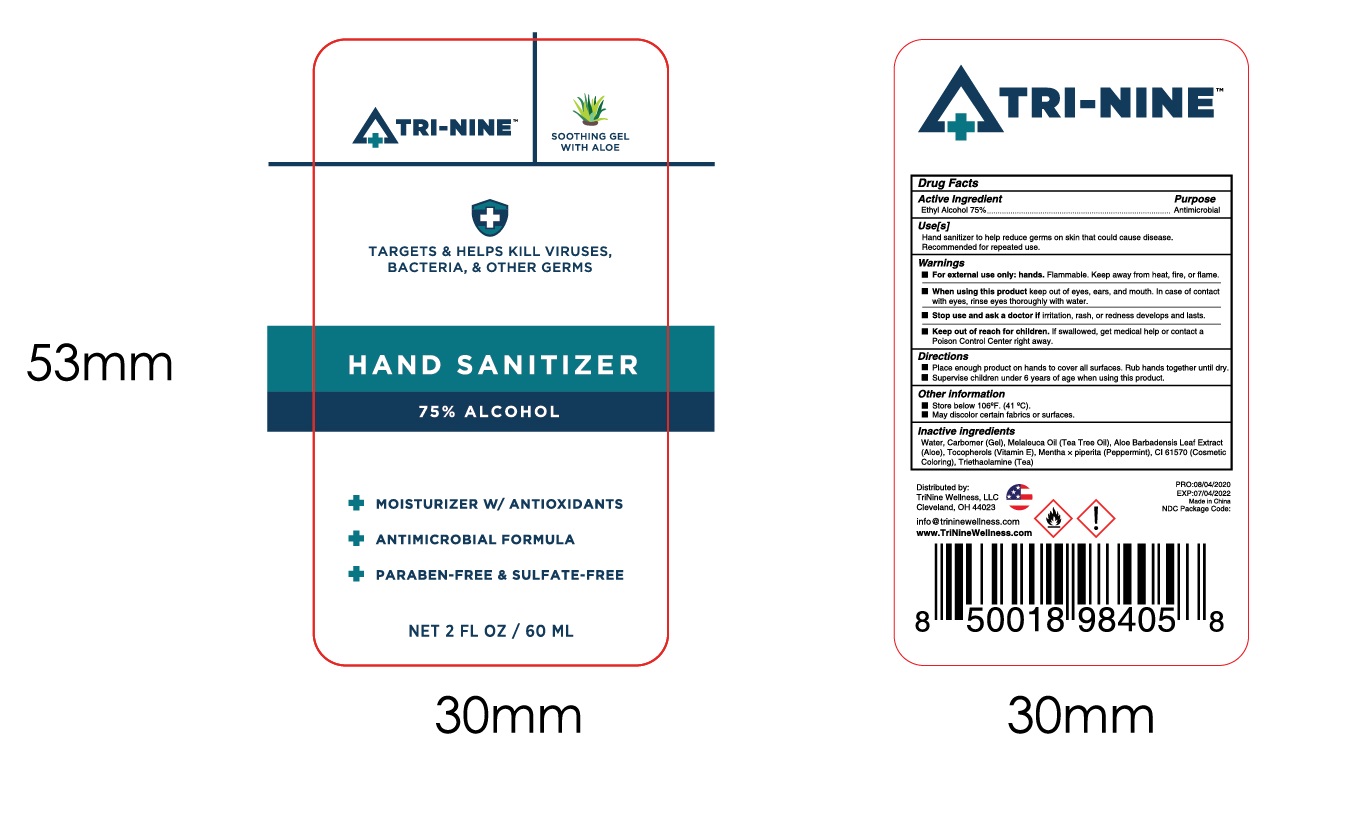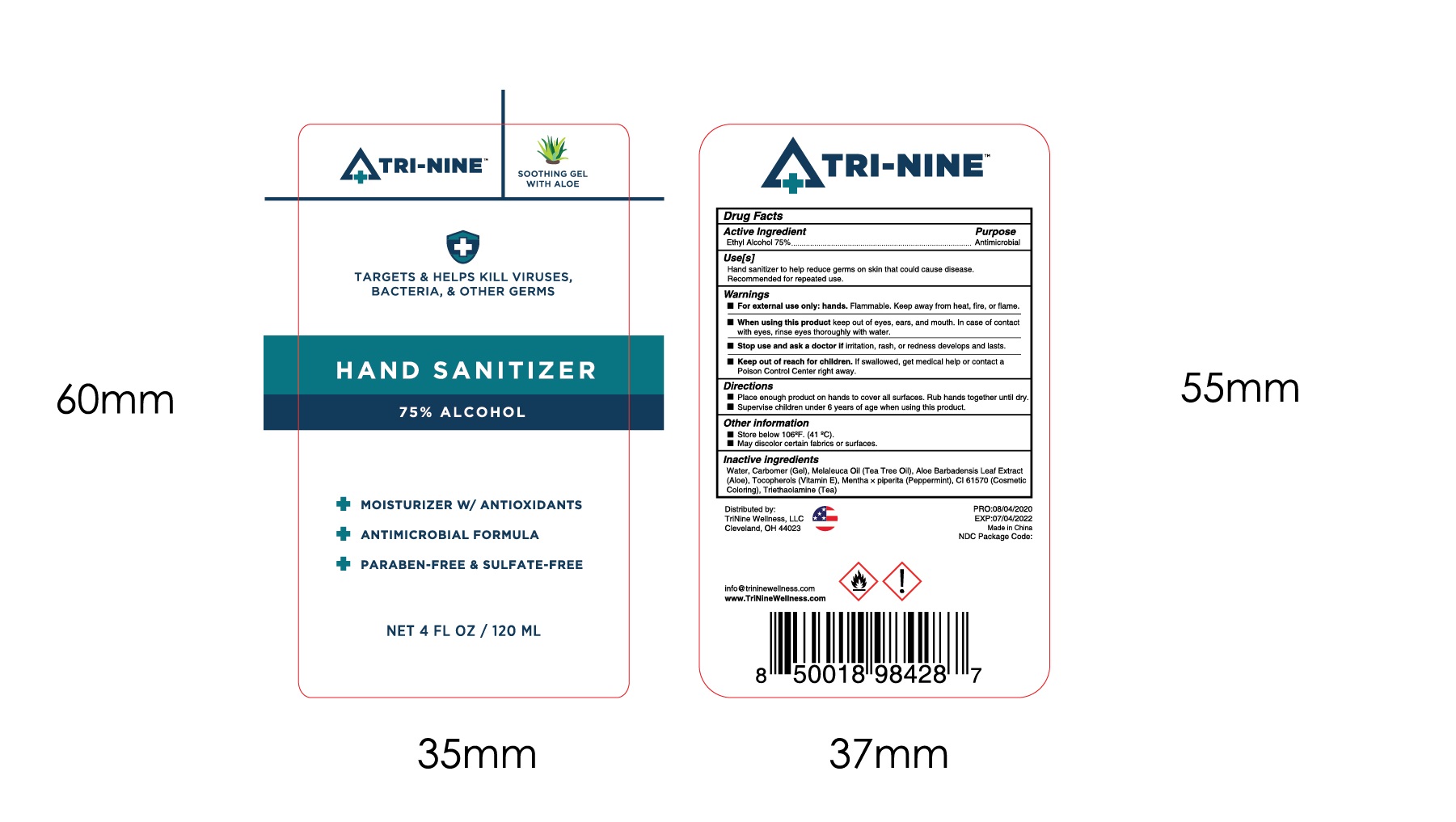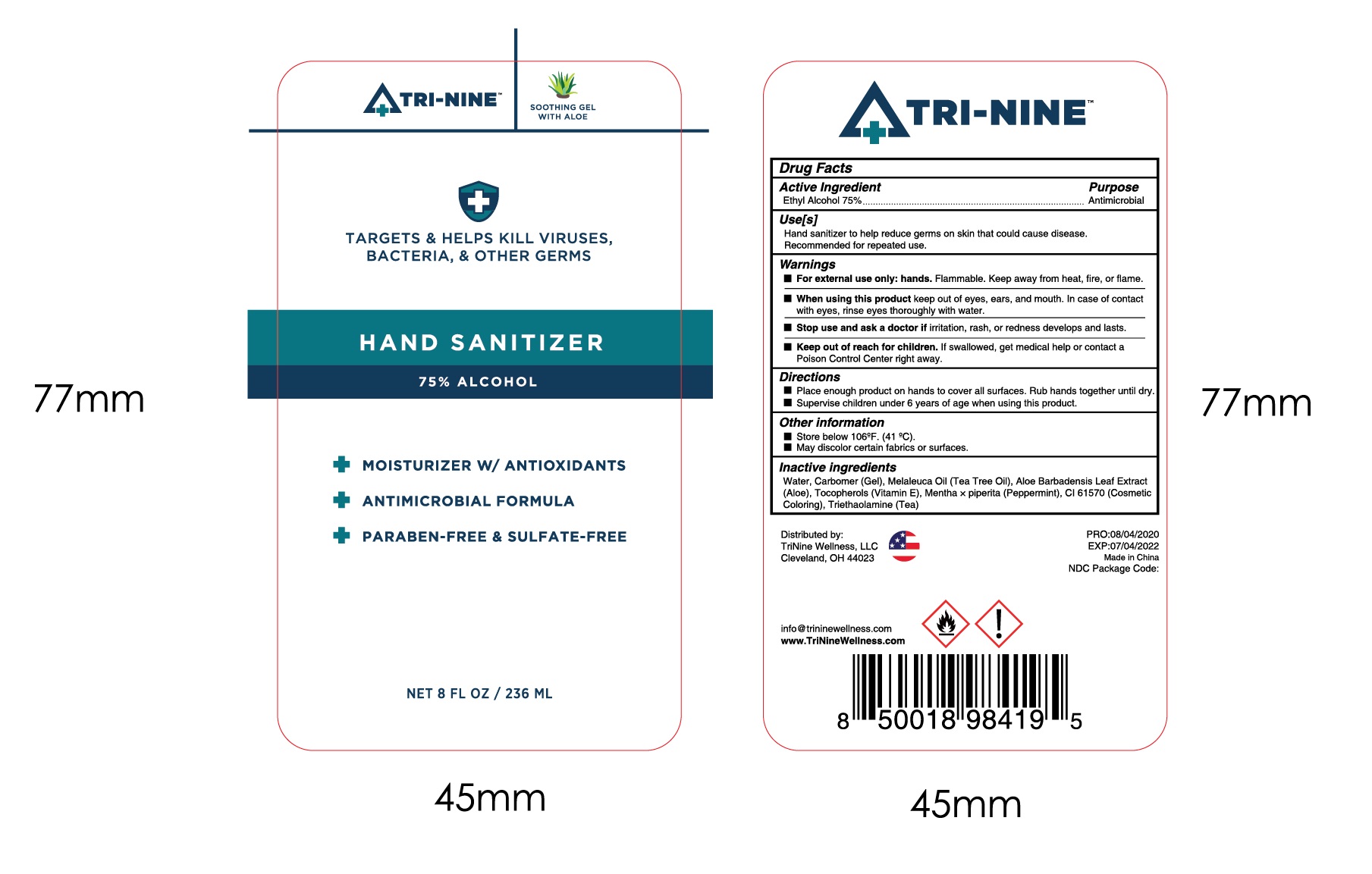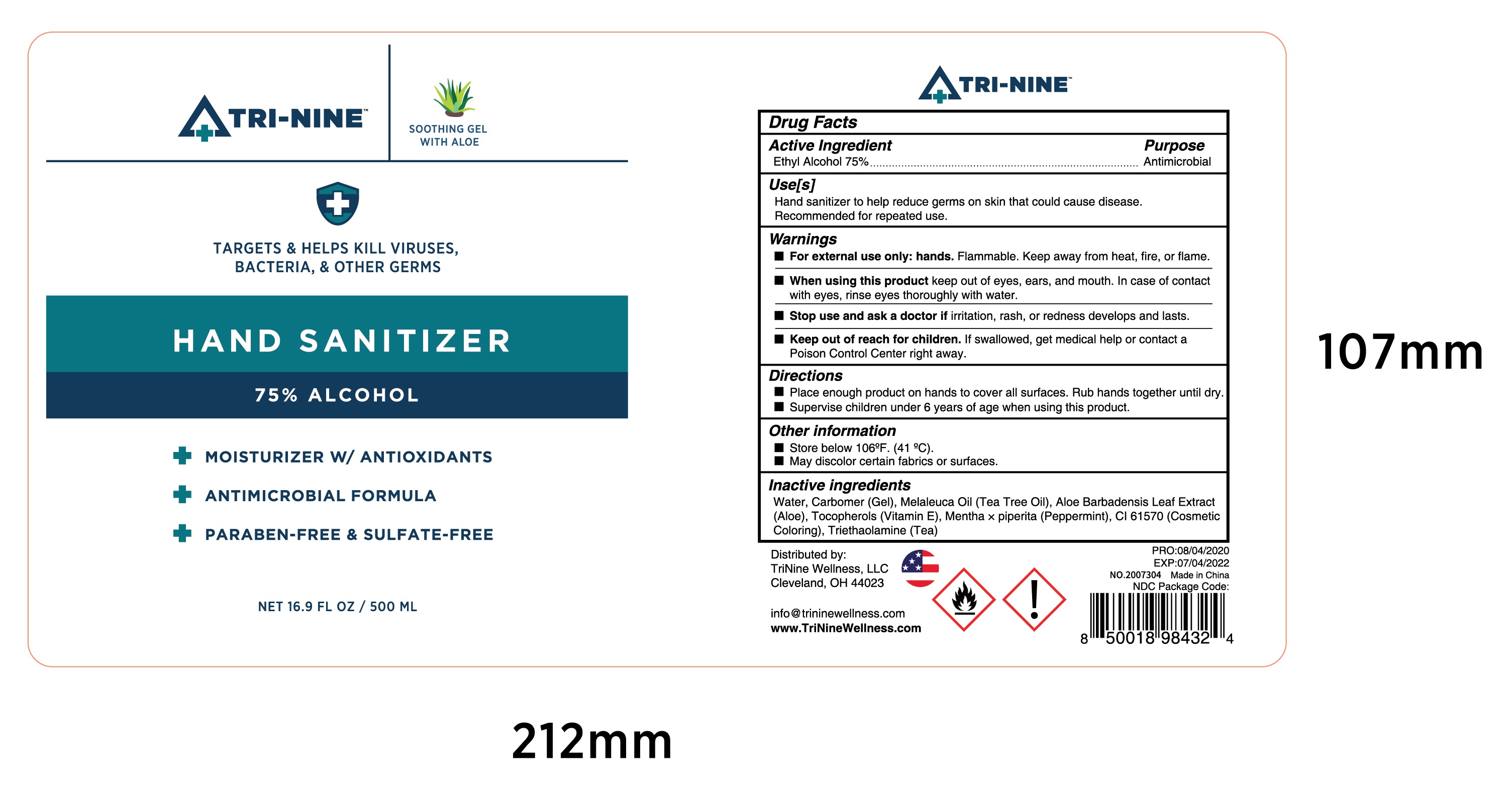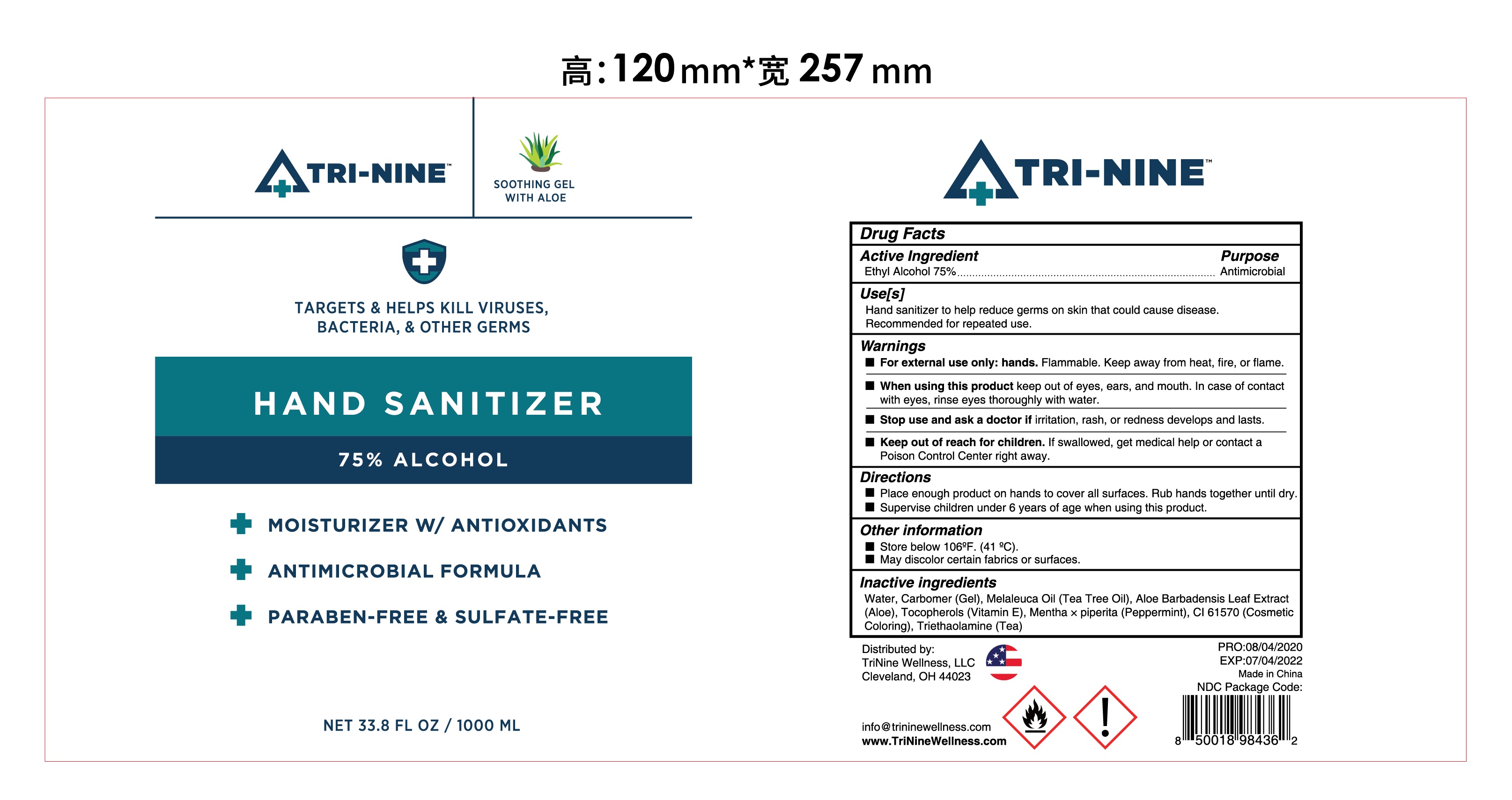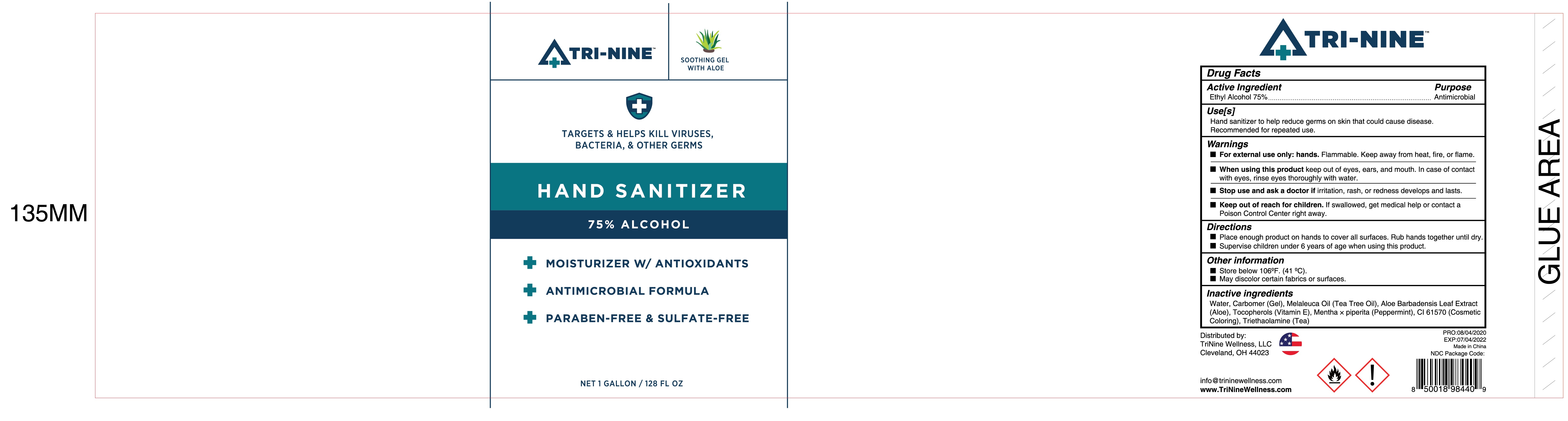 DRUG LABEL: Hand Sanitizer
NDC: 79054-004 | Form: GEL
Manufacturer: TRININE WELLNESS LLC
Category: otc | Type: HUMAN OTC DRUG LABEL
Date: 20200818

ACTIVE INGREDIENTS: ALCOHOL 75 mL/100 mL
INACTIVE INGREDIENTS: CARBOMER HOMOPOLYMER, UNSPECIFIED TYPE; TEA TREE OIL; WATER; TROLAMINE; TOCOPHEROL; ALOE VERA LEAF; D&C GREEN NO. 5; PEPPERMINT

004 Hand sanitizer

Active Ingredient(s)

Ethyl Alcohol 75%

Purpose

Antimicrobial

Use

Hand sanitizer to help reduce germs on skin that could cause disease.

Recommended for repeated use.

Warnings

For external use only: hands.Flammable. Keep away from heat, fire, or flame.

When using this product keep out of eyes, ears, and mouth. In case of contact

with eyes, rinse eyes thoroughly with water.

Stop use and ask a doctor if irritation, rash, or redness develops and lasts.

Keep out of reach for children. If swallowed, get medical help or contact a

Poison Control Center right away.

Do not use

/

When using this product keep out of eyes, ears, and mouth. In case of contact

with eyes, rinse eyes thoroughly with water.

Stop use and ask a doctor if irritation, rash, or redness develops and lasts.

KEEP OUT OF REACH OF CHILDREN

Keep out of reach for children. If swallowed, get medical help or contact a

Poison Control Center right away.

Directions

Place enough product on hands to cover all surfaces. Rub hands together until dry.

Supervise children under 6 years of age when using this product.

Other information

Store below 106ºF. (41 ºC).

May discolor certain fabrics or surfaces.

Inactive ingredients

Water, Carbomer (Gel), Melaleuca Oil (Tea Tree Oil), Aloe Barbadensis Leaf Extract

(Aloe), Tocopherols (Vitamin E), Mentha × piperita (Peppermint), CI 61570 (Cosmetic Coloring), Triethaolamine (Tea)